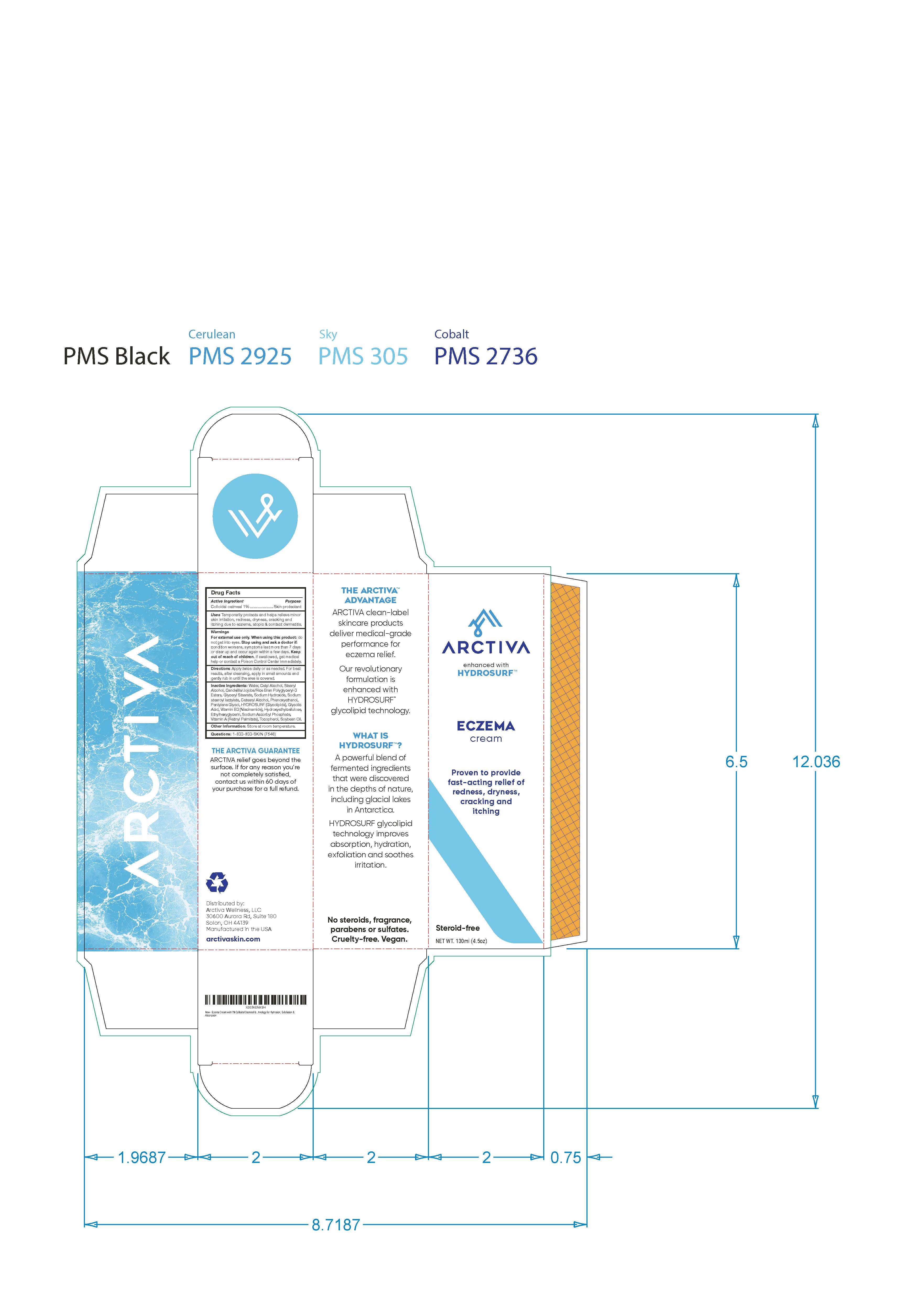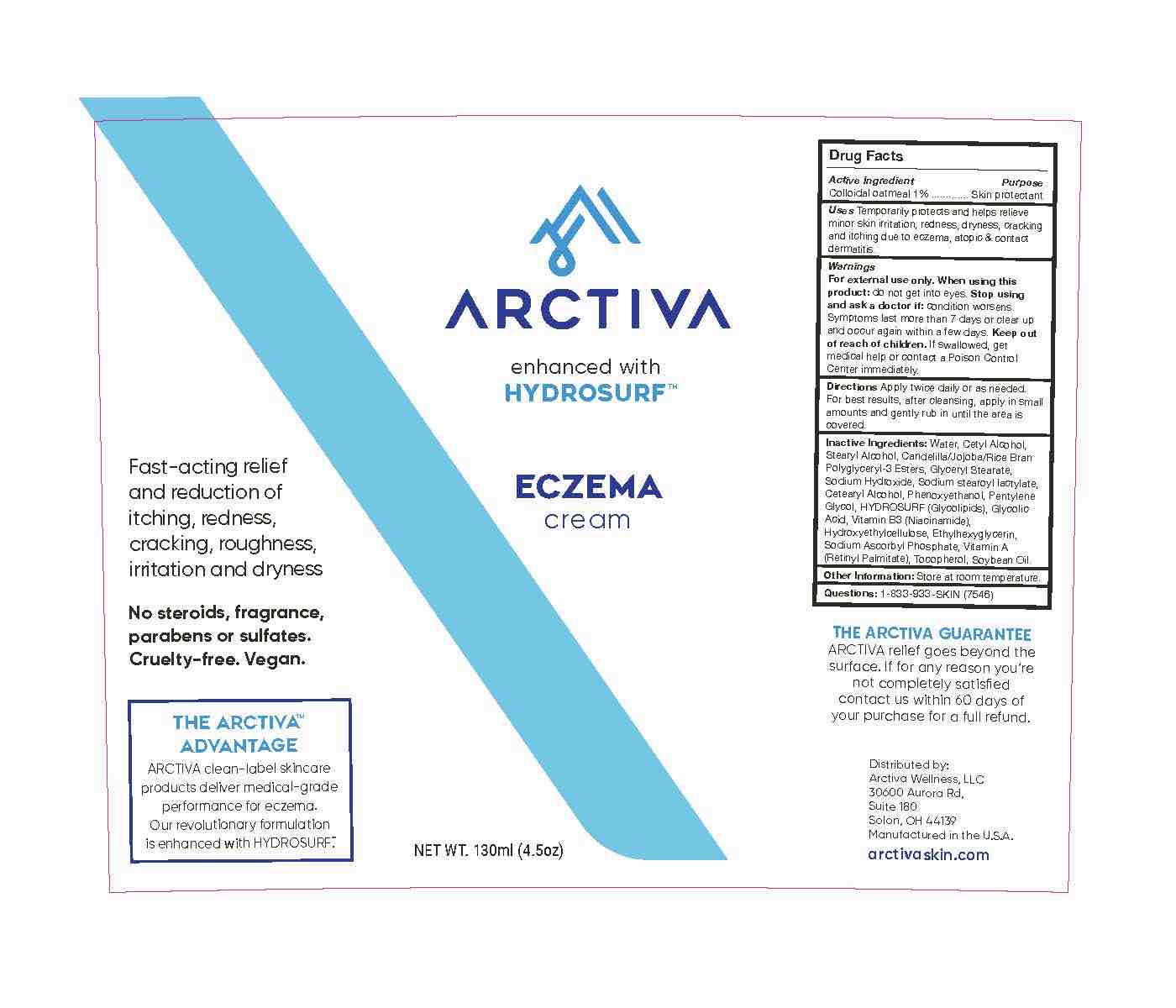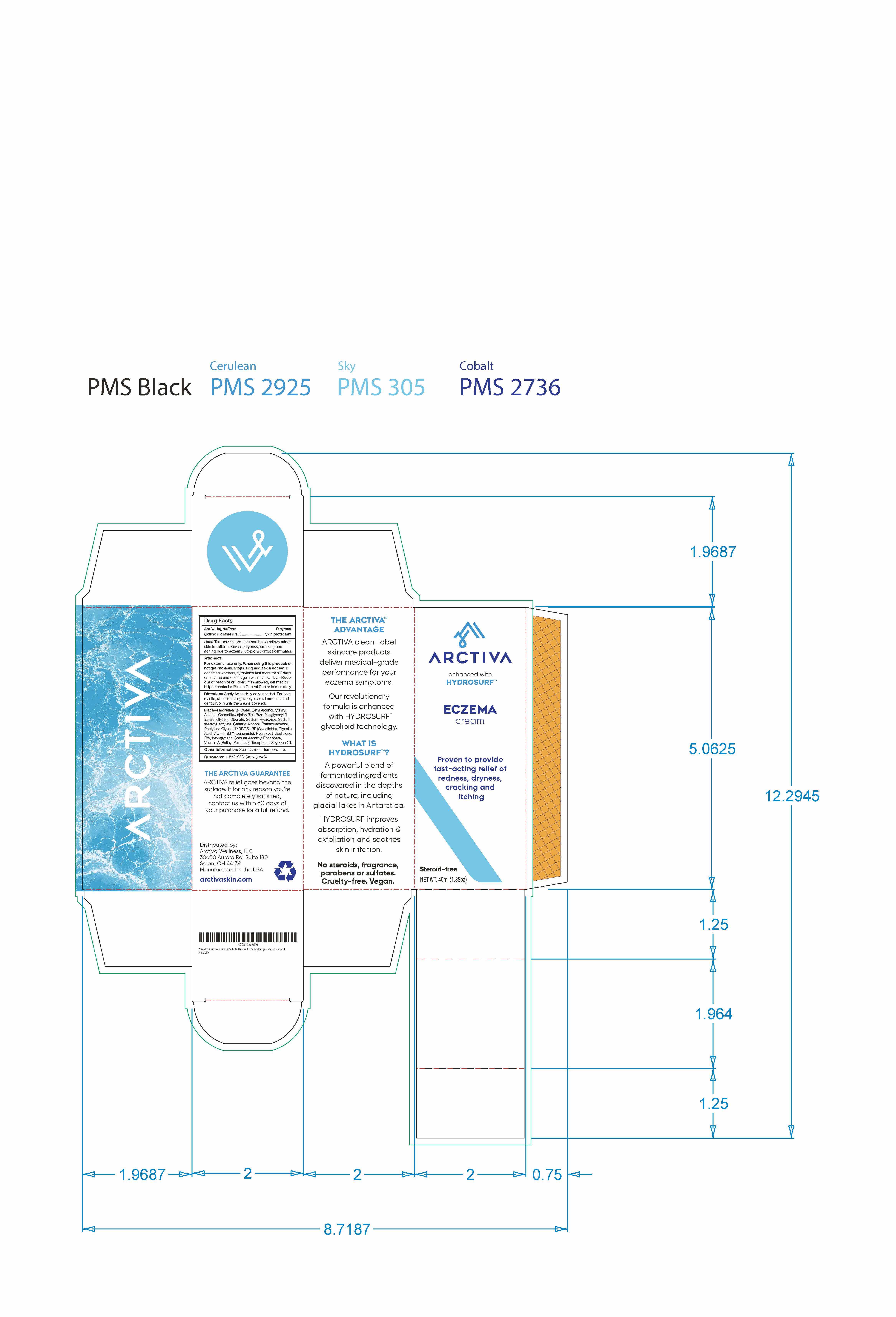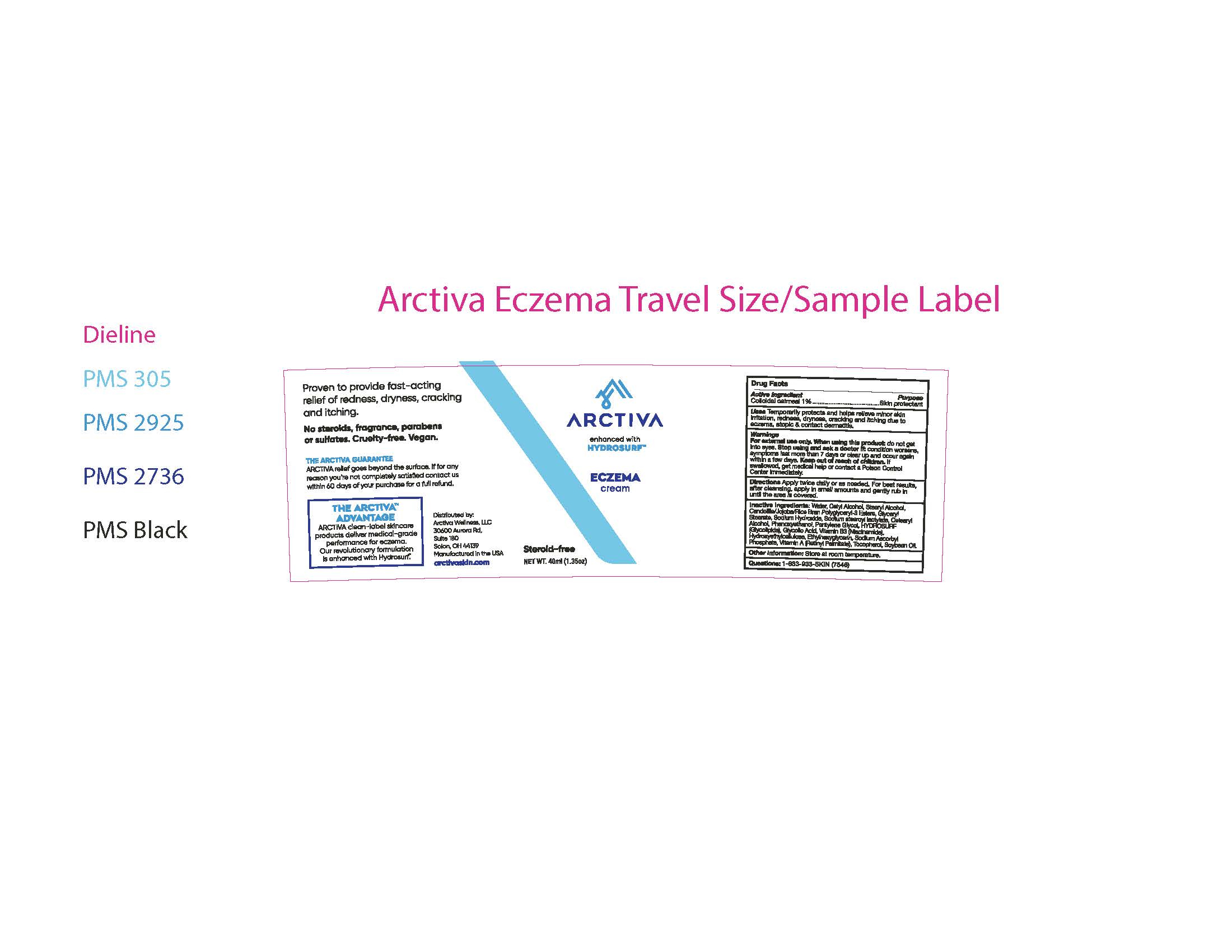 DRUG LABEL: Arctiva Eczema Cream
NDC: 58418-821 | Form: CREAM
Manufacturer: Epic Laboratories, LLC
Category: otc | Type: HUMAN OTC DRUG LABEL
Date: 20250127

ACTIVE INGREDIENTS: OATMEAL 1 g/130 mL
INACTIVE INGREDIENTS: JOJOBA OIL, RANDOMIZED; CETOSTEARYL ALCOHOL; NIACINAMIDE; HYDROXYETHYL CELLULOSE (280 MPA.S AT 2%); SODIUM STEAROYL LACTYLATE; GLYCERYL MONOSTEARATE; RICE BRAN; POLYGLYCERIN-3; WATER; SODIUM HYDROXIDE; SODIUM ASCORBYL PHOSPHATE; CETYL ALCOHOL; STEARYL ALCOHOL; VITAMIN A PALMITATE; PHENOXYETHANOL; PENTYLENE GLYCOL; GLYCOLIC ACID; ETHYLHEXYLGLYCERIN; CANDELILLA WAX; LIPID A 504

Arctiva Eczema Cream

Active Ingredient
Colloidal oatmeal 1%......

Purpose... Skin protectant

INDICATIONS AND USAGE

Uses: Temporarily protects and helps relieve minor skin irritations, redness, dryness, cracking and itching

due to eczema and dermatitis.

Warnings

For external use only. When using this product: do not get into eyes.

Stop using and ask a doctor if: condition worsen, symptoms last more

than 7 days or clear up and occur again within a few days.

Keep out of reach of children. If swallowed, get medical help or contact

a Poison. Control Center immediately.

DOSAGE AND ADMINISTRATION

Directions Apply twice daily or as needed.
For best results apply after cleansing.

Inactive Ingredients: Water, Cetyl Alcohol, Stearyl Alcohol,

Candelila/Jojoba/Rice Bran Polyglyceryl-3 esters, Glyceryl Stearate,
Sodium Hydroxide, Sodium stearoyl lactylate,Cetearyl Alcohol, Phenoxyethanol, Pentylene Glycol,

Hydrosuf (Glycolipids), Glycolic Acid, Vitamin B3 (Niacinamide), Hydroxyethylcellulose, Ethylhexyglycerin,

Sodium Ascorbyl Phosphate, Vitamin A (Retinyl Palmitate), Tocopherol, Soybean Oil.

Other Information: Store at room temperature.

Questions: 1-833-933-SKIN (7546)

THE ARCTIVA GUARANTEE

Arctiva relief goes beyond the surface. If for any reason you're

not completely satisfied contact us within 60 days of your purchase

for a full refund.

Distributed by:

Arctiva Wellness, LLC

30600 Aurora Rd.

Suite 180

Salon, OH 44139

Made in U.S.A

arctivaskin.com